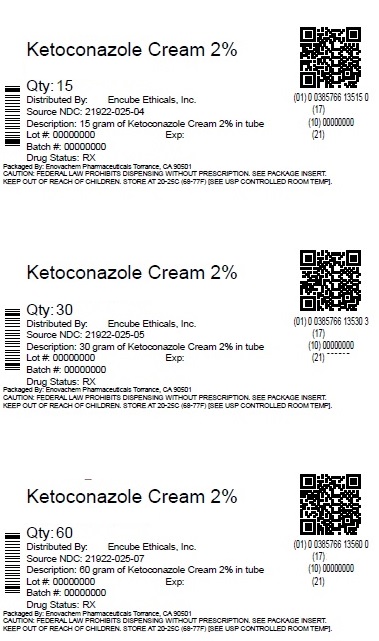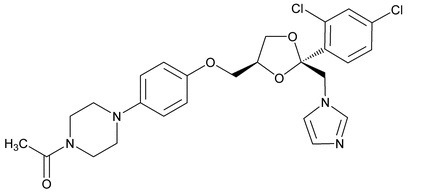 DRUG LABEL: Ketoconazole
NDC: 87063-066 | Form: CREAM
Manufacturer: ASCLEMED USA INC.
Category: prescription | Type: HUMAN PRESCRIPTION DRUG LABEL
Date: 20260123

ACTIVE INGREDIENTS: KETOCONAZOLE 20 mg/1 g
INACTIVE INGREDIENTS: PROPYLENE GLYCOL; WATER; CETYL ALCOHOL; STEARYL ALCOHOL; ISOPROPYL MYRISTATE; SORBITAN MONOSTEARATE; POLYSORBATE 60; POLYSORBATE 80; SODIUM SULFITE

KETOCONAZOLE CREAM
Rx only

DESCRIPTION

Ketoconazole Cream, 2% contains the broad-spectrum synthetic antifungal agent, ketoconazole 2%. Each gram, for topical administration, contains ketoconazole 20 mg and is formulated in an aqueous cream vehicle consisting of propylene glycol, purified water, cetyl alcohol, stearyl alcohol, isopropyl myristate, sorbitan monostearate, polysorbate 60, polysorbate 80, and sodium sulfite, anhydrous:

Ketoconazole is cis-1-acetyl-4-[4-[[2-(2,4-dichlorophenyl)-2-(1H-imidazol-1-ylmethyl)-1,3-dioxolan-4-yl]methoxy]phenyl] piperazine and has the following structural formula:

M. Formula: C26H28Cl2N4O4 M.W.: 531.44

CLINICAL PHARMACOLOGY

When Ketoconazole Cream, 2% was applied dermally to intact or abraded skin of Beagle dogs for 28 consecutive days at a dose of 80 mg, there were no detectable plasma levels using an assay method having a lower detection limit of 2 ng/ml.

After a single topical application to the chest, back and arms of normal volunteers, systemic absorption of ketoconazole was not detected at the 5 ng/ml level in blood over a 72-hour period.

Two dermal irritancy studies, a human sensitization test, a phototoxicity study and a photoallergy study conducted in 38 male and 62 female volunteers showed no contact sensitization of the delayed hypersensitivity type, no irritation, no phototoxicity and no photoallergenic potential due to Ketoconazole Cream, 2%.
Microbiology:

Ketoconazole is a broad spectrum synthetic antifungal agent which inhibits the in vitro growth of the following common dermatophytes and yeasts by altering the permeability of the cell membrane: dermatophytes: Trichophyton rubrum, T. mentagrophytes, T. tonsurans, Microsporum canis, M. audouini, M. gypseum and Epidermophyton floccosum; yeasts: Candida albicans , Malassezia ovale (Pityrosporum ovale)and C. tropicalis; and the organism responsible for tinea versicolor, Malassezia furfur (Pityrosporum orbiculare). Only those organisms listed in the INDICATIONS AND USAGE Section have been proven to be clinically affected. Development of resistance to ketoconazole has not been reported.
Mode of Action:

In vitrostudies suggest that ketoconazole impairs the synthesis of ergosterol, which is a vital component of fungal cell membranes. It is postulated that the therapeutic effect of ketoconazole in seborrheic dermatitis is due to the reduction of M. ovale, but: this has not been proven.

INDICATIONS AND USAGE

Ketoconazole Cream, 2% is indicated for the topical treatment of tinea corporis, tinea cruris and tinea pedis caused by Trichophyton rubrum, T. mentagrophytesand Epidermophyton floccosum; in the treatment of tinea (pityriasis) versicolor caused by Malassezia furfur (Pityrosporum orbiculare); and in the treatment of cutaneous candidiasis caused by Candida spp. and in the treatment of seborrheic dermatitis.

CONTRAINDICATIONS

Ketoconazole Cream, 2% is contraindicated in persons who have shown hypersensitivity to the active or excipient ingredients of this formulation.

WARNINGS

Ketoconazole Cream, 2% is not for ophthalmic use.

Ketoconazole Cream, 2% contains sodium sulfite anhydrous, a sulfite that may cause allergic-type reactions including anaphylactic symptoms and life-threatening or less severe asthmatic episodes in certain susceptible people. The overall prevalence of sulfite sensitivity in the general population is unknown and probably low. Sulfite sensitivity is seen more frequently in asthmatic than in nonasthmatic people.

PRECAUTIONS

General

If a reaction suggesting sensitivity or chemical irritation should occur, use of the medication should be discontinued. Hepatitis (1:10,000 reported incidence) and, at high doses, lowered testosterone and ACTH induced corticosteroid serum levels have been seen with orally administered ketoconazole; these effects have not been seen with topical ketoconazole.

Carcinogenesis, Mutagenesis, Impairment of Fertility

A long-term feeding study in Swiss Albino mice and in Wistar rats showed no evidence of oncogenic activity. The dominant lethal mutation test in male and female mice revealed that single oral doses of ketoconazole as high as 80 mg/kg produced no mutation in any stage of germ cell development. The Ames' Salmonellamicrosomal activator assay was also negative.

Pregnancy

Teratogenic effects

Pregnancy Category C

Ketoconazole has been shown to be teratogenic (syndactylia and oligodactylia) in the rat when given orally in the diet at 80 mg/kg/day, (10 times the maximum recommended human oral dose). However, these effects may be related to maternal toxicity, which was seen at this and higher dose levels.

There are no adequate and well-controlled studies in pregnant women. Ketoconazole should be used during pregnancy only if the potential benefit justifies the potential risk to the fetus.

Nursing Mothers

It is not known whether Ketoconazole Cream, 2% administered topically could result in sufficient systemic absorption to produce detectable quantities in breast milk. Nevertheless, a decision should be made whether to discontinue nursing or discontinue the drug, taking into account the importance of the drug to the mother.

Pediatric Use

Safety and effectiveness in children have not been established.

ADVERSE REACTIONS

During clinical trials 45 (5%) of 905 patients treated with Ketoconazole Cream, 2% and 5 (2.4%) of 208 patients treated with placebo reported side effects consisting mainly of severe irritation, pruritus and stinging. One of the patients treated with ketoconazole cream developed a painful allergic reaction.

In worldwide postmarketing experience, rare reports of contact dermatitis have been associated with ketoconazole cream or one of its excipients, namely sodium sulfite or propylene glycol.
To report SUSPECTED ADVERSE REACTIONS, contact Encube Ethicals Private Limited at 1-833-285-4151 or FDA at 1-800- FDA-1088 or www.fda.gov/medwatch.

DOSAGE AND ADMINISTRATION

Cutaneous candidiasis, tinea corporis, tinea cruris, tinea pedis, and tinea (pityriasis) versicolor:It is recommended that Ketoconazole Cream, 2% be applied once daily to cover the affected and immediate surrounding area. Clinical improvement may be seen fairly soon after treatment is begun; however, candidal infections and tinea cruris and corporis should be treated for two weeks in order to reduce the possibility of recurrence. Patients with tinea versicolor usually require two weeks of treatment .Patients with tinea pedis require six weeks of treatment.

Seborrheic dermatitis: Ketoconazole cream, 2% should be applied to the affected area twice daily for four weeks or until no clinical clearing.

If a patient shows no clinical improvement after the treatment period, the diagnosis should be redetermined.

HOW SUPPLIED

Ketoconazole Cream, 2% is supplied in 15, 30, and 60 gram tubes.

15 g tube (NDC 87063-066-15 relabeled from NDC 21922-025-04)

30 g tube (NDC 87063-066-30 relabeled from NDC 21922-025-05)

60 g tube (NDC 87063-066-60 relabeled from NDC 21922-025-07)

STORAGE

Store at 20° to 25°C (68° to 77°F) [see USP Controlled Room Temperature].

Relabeled by:

Enovachem PHARMACEUTICALS

Torrance, CA 90501